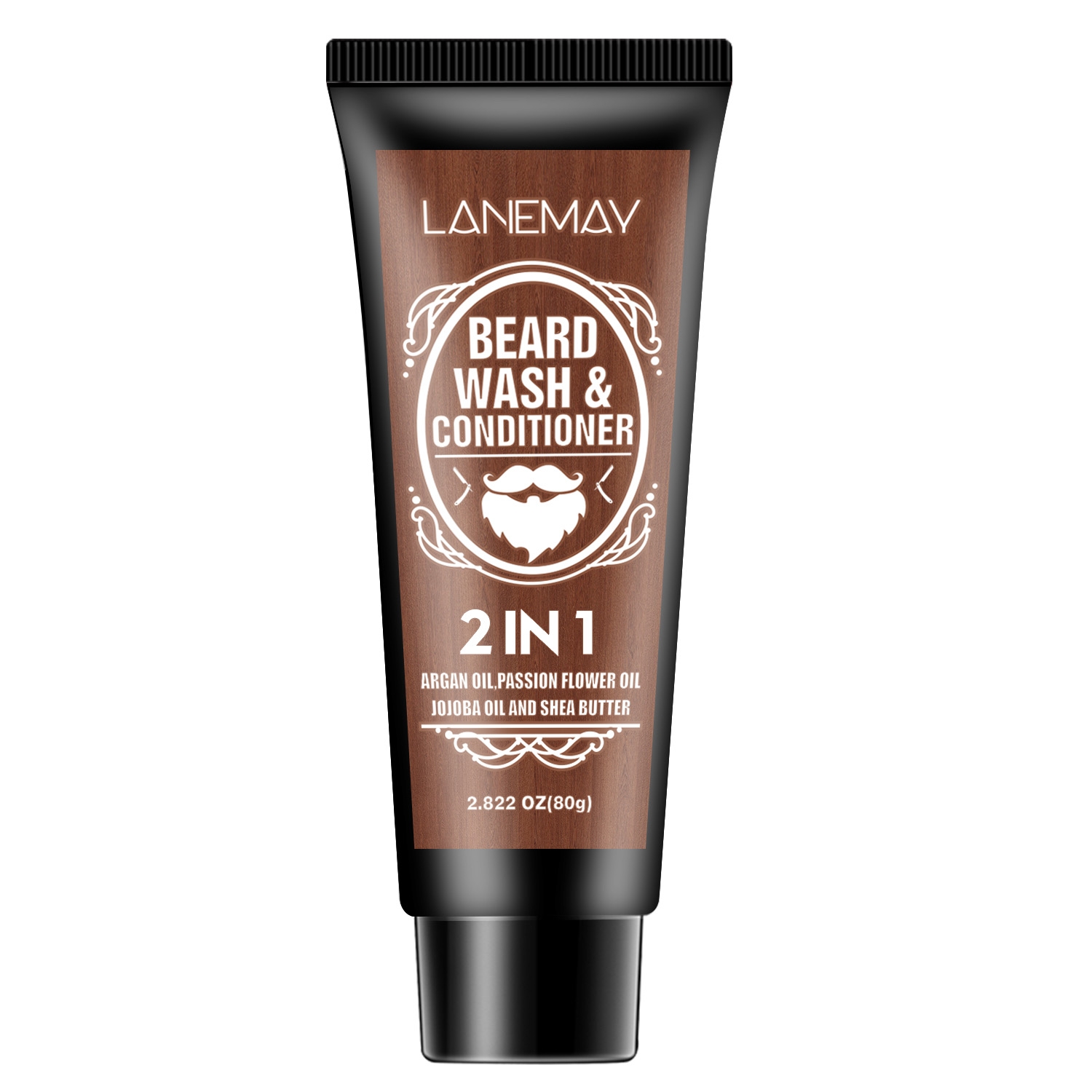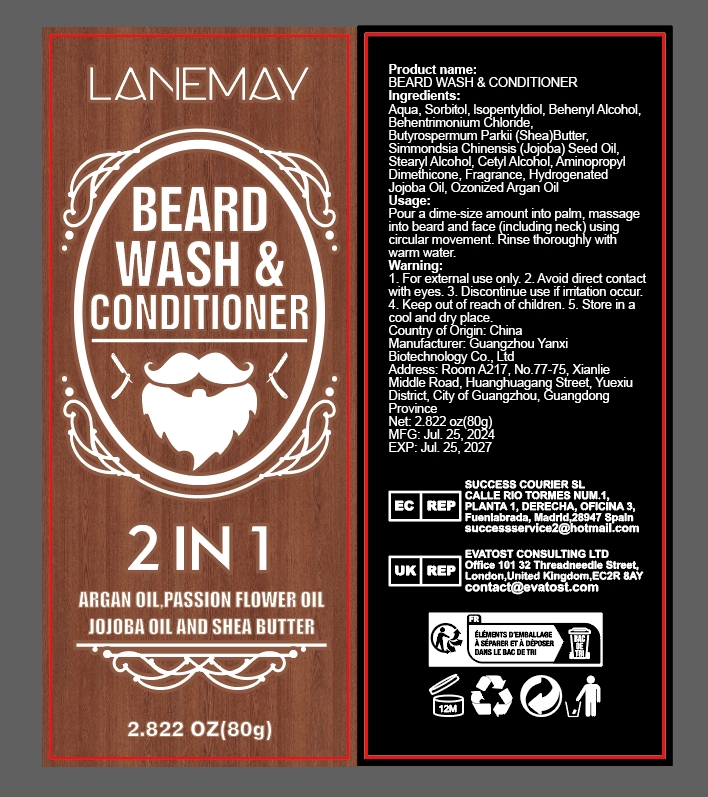 DRUG LABEL: Beard Wash Conditioner
NDC: 84025-161 | Form: CREAM
Manufacturer: Guangzhou Yanxi Biotechnology Co.. Ltd
Category: otc | Type: HUMAN OTC DRUG LABEL
Date: 20240818

ACTIVE INGREDIENTS: SORBITOL 5 mg/80 g; STEARYL ALCOHOL 3 mg/80 g
INACTIVE INGREDIENTS: WATER

DOSAGE AND ADMINISTRATION

Conditioner for cleaning and caring for the beard

WARNINGS

Keep out of children

INACTIVE INGREDIENT

AQUA

INDICATIONS AND USAGE

For daily beard care

Keep out of children

PURPOSE

Moisturizes and maintains the beard, keeping the beard hair smooth